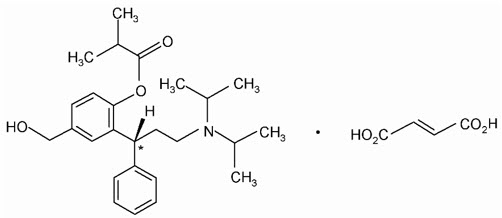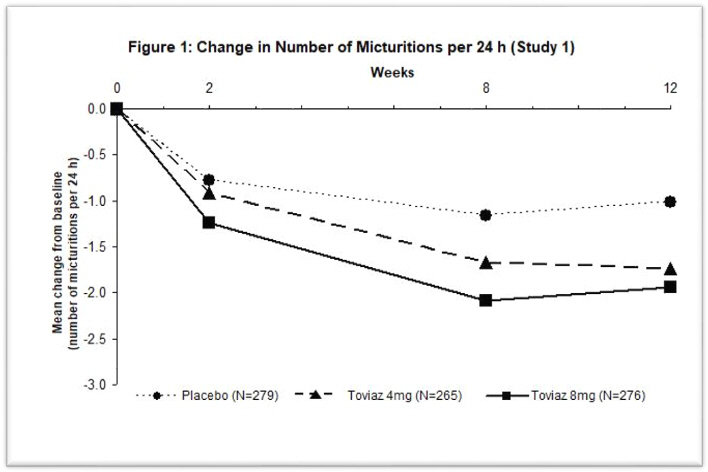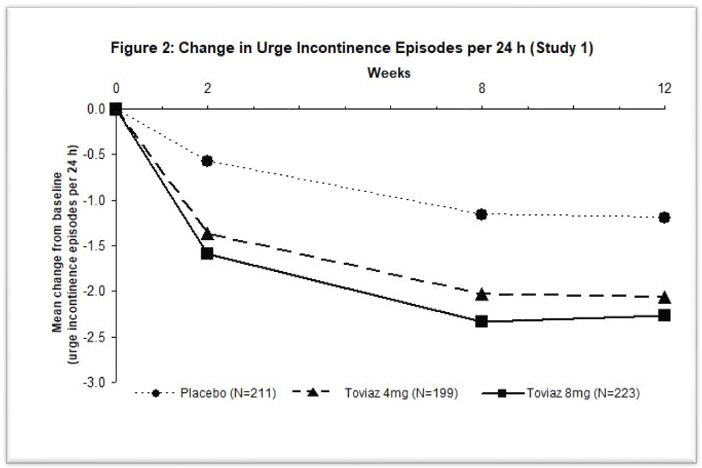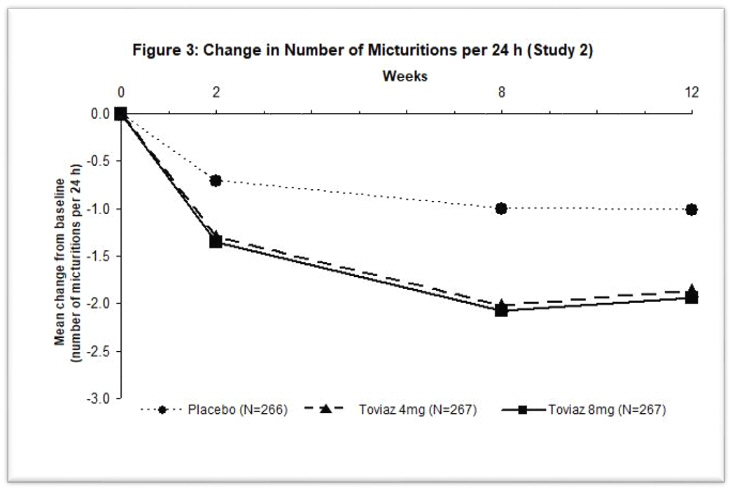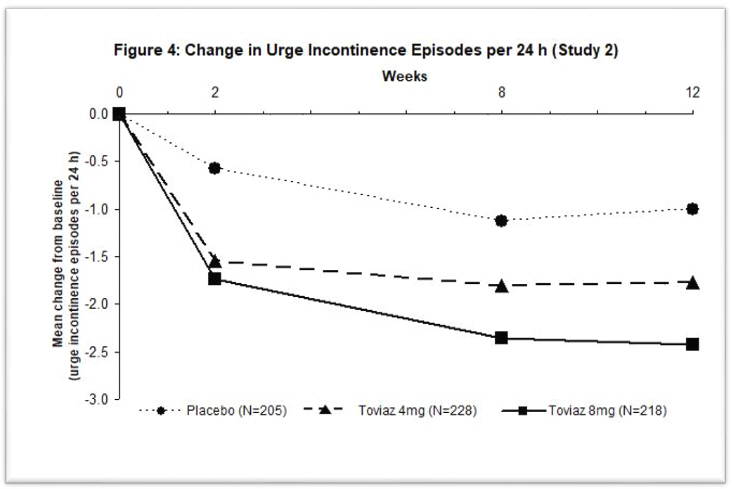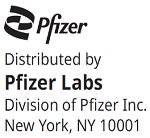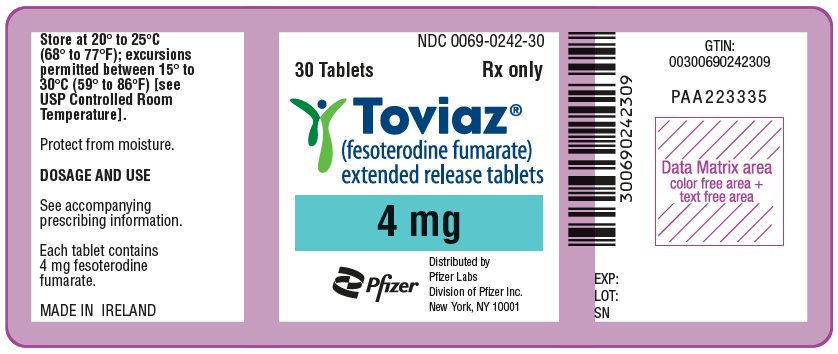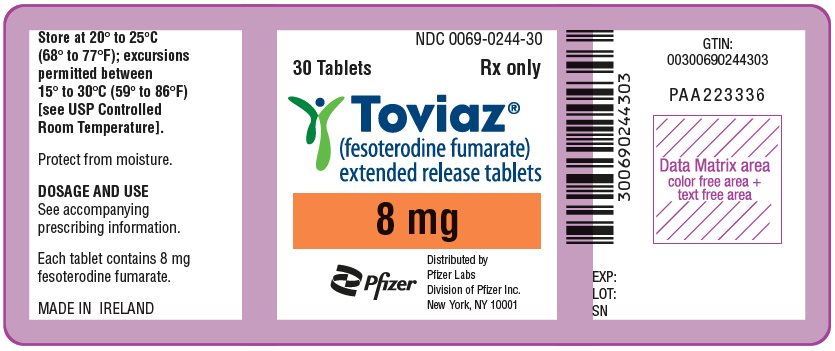 DRUG LABEL: Toviaz
NDC: 0069-0242 | Form: TABLET, FILM COATED, EXTENDED RELEASE
Manufacturer: Pfizer Laboratories Div Pfizer Inc
Category: prescription | Type: HUMAN PRESCRIPTION DRUG LABEL
Date: 20241212

ACTIVE INGREDIENTS: FESOTERODINE FUMARATE 4 mg/1 1
INACTIVE INGREDIENTS: GLYCERYL DIBEHENATE; HYPROMELLOSE, UNSPECIFIED; INDIGOTINDISULFONATE SODIUM; ALUMINUM OXIDE; LACTOSE MONOHYDRATE; SOYBEAN LECITHIN; MICROCRYSTALLINE CELLULOSE; POLYETHYLENE GLYCOL, UNSPECIFIED; POLYVINYL ALCOHOL, UNSPECIFIED; TALC; TITANIUM DIOXIDE; XYLITOL

HIGHLIGHTS OF PRESCRIBING INFORMATION

These highlights do not include all the information needed to use TOVIAZ safely and effectively. See full prescribing information for TOVIAZ.
TOVIAZ® (fesoterodine fumarate) extended-release tablets, for oral use
Initial U.S. Approval: 2008

1 INDICATIONS AND USAGE

Toviaz is indicated for the treatment of:

- Overactive bladder (OAB) in adults with symptoms of urge urinary incontinence, urgency, and frequency. (1.1)
- Neurogenic detrusor overactivity (NDO) in pediatric patients 6 years of age and older and weighing greater than 25 kg. (1.2)

2 DOSAGE AND ADMINISTRATION

- OAB in Adults: The recommended starting dosage is 4 mg orally once daily. Based upon individual response and tolerability, increase to the maximum dosage of 8 mg once daily. (2.1)
- NDO in Pediatric Patients 6 Years and Older:
  - Pediatric Patients Weighing Greater than 25 kg and up to 35 kg:
    The recommended dosage is 4 mg orally once daily. If needed, dosage may be increased to 8 mg orally once daily. (2.2)
  - Pediatric Patients Weighing Greater than 35 kg:
    The recommended starting dosage is 4 mg orally once daily. After one week, increase to 8 mg orally once daily. (2.2)
- Adult or Pediatric Patients with Renal Impairment: Refer to the full prescribing information for recommended dosage. (2.3, 2.4)
- Dosage Modifications Due to Strong CYP3A4 Inhibitors: Refer to the full prescribing information for recommended dosage. (2.5)
- Administration: Swallow whole with liquid. Do not chew, divide, or crush. Take with or without food. (2.6)

3 DOSAGE FORMS AND STRENGTHS

Extended-release tablets: 4 mg and 8 mg (3)

4 CONTRAINDICATIONS

- Known or suspected hypersensitivity to Toviaz or any of its ingredients or to tolterodine tartrate tablets or tolterodine tartrate extended-release capsules. (4)
- Urinary retention (4)
- Gastric retention (4)
- Uncontrolled narrow-angle glaucoma. (4)

5 WARNINGS AND PRECAUTIONS

- Angioedema: Promptly discontinue Toviaz and provide appropriate therapy. (5.1)
- Urinary Retention: Toviaz is not recommended in patients with clinically significant bladder outlet obstruction because of the risk of urinary retention. (5.2)
- Decreased Gastrointestinal Motility: Toviaz is not recommended for use in patients with decreased gastrointestinal motility, such as those with severe constipation. (5.3)
- Worsening of Narrow-Angle Glaucoma: Use Toviaz with caution in patients being treated for narrow-angle glaucoma. (5.4)
- Central Nervous System Effects: Somnolence has been reported with Toviaz. Advise patients not to drive or operate heavy machinery until they know how Toviaz affects them. (5.5)
- Worsening of Myasthenia Gravis Symptoms: Use Toviaz with caution in patients with myasthenia gravis. (5.6)

6 ADVERSE REACTIONS

- Most frequently reported adverse events with Toviaz in adult patients with OAB (≥4%) were: dry mouth (placebo, 7%; Toviaz 4 mg, 19%; Toviaz 8 mg, 35%) and constipation (placebo, 2%; Toviaz 4 mg, 4%; Toviaz 8 mg, 6%). (6.1)
- Most frequently reported adverse reactions with Toviaz in pediatric patients (≥2%) with NDO were: diarrhea, urinary tract infection (UTI), dry mouth, constipation, abdominal pain, nausea, weight increased, and headache. (6.1)

To report SUSPECTED ADVERSE REACTIONS, contact Pfizer Inc. at 1-800-438-1985 or FDA at 1-800-FDA-1088 or www.fda.gov/medwatch.

FULL PRESCRIBING INFORMATION

1 INDICATIONS AND USAGE

1.1 Adult Overactive Bladder

Toviaz is indicated for the treatment of overactive bladder (OAB) in adults with symptoms of urge urinary incontinence, urgency, and frequency.

1.2 Pediatric Neurogenic Detrusor Overactivity

Toviaz is indicated for the treatment of neurogenic detrusor overactivity (NDO) in pediatric patients 6 years of age and older with a body weight greater than 25 kg.

2 DOSAGE AND ADMINISTRATION

2.1 Recommended Dosage for Adult Patients With OAB

The recommended starting dosage of Toviaz in adults is 4 mg orally once daily. Based upon individual response and tolerability, increase to the maximum dosage of Toviaz 8 mg once daily. For administration instructions, see Dosage and Administration (2.6).

2.2 Recommended Dosage for Pediatric Patients Aged 6 Years and Older With NDO

Pediatric Patients Weighing Greater than 25 kg and up to 35 kg

The recommended dosage of Toviaz is 4 mg orally once daily. If needed, dosage may be increased to Toviaz 8 mg orally once daily. For administration instructions, see Dosage and Administration (2.6).

Pediatric Patients Weighing Greater than 35 kg

The recommended starting dosage of Toviaz is 4 mg orally once daily. After one week, increase to Toviaz 8 mg orally once daily. For administration instructions, see Dosage and Administration (2.6).

2.3 Recommended Dosage in Adult Patients With Renal Impairment

The recommended dosage of Toviaz in adult patients with renal impairment is described in Table 1 [see Use in Specific Populations (8.6)]. For administration instructions, see Dosage and Administration (2.6).

Table 1: Toviaz Recommended Dose in Adult Patients With Renal Impairment (Administered Orally Once Daily)
Estimated Creatinine Clearance [Calculate CLcr using the Cockcroft-Gault formula] | Recommended Dose
CLcr 30 to 89 mL/min | 8 mg
CLcr 15 to 29 mL/min | 4 mg
CLcr <15 mL/min | 4 mg

2.4 Recommended Dosage in Pediatric Patients With Renal Impairment

Pediatric Patients Weighing Greater than 25 kg and up to 35 kg

The recommended dosage of Toviaz in pediatric patients with renal impairment weighing greater than 25 kg and up to 35 kg is described in Table 2 [see Use in Specific Populations (8.6)]. For administration instructions, see Dosage and Administration (2.6).

Table 2: Toviaz Recommended Dose in Pediatric Patients Aged 6 Years and Older Weighing Greater Than 25 kg and up to 35 kg With Renal Impairment (Administered Orally Once Daily)
Estimated Glomerular Filtration Rate (GFR) [Estimate GFR using a validated GFR estimating equation for the pediatric age range of the approved indication.] | Recommended Dose [Dosing was derived assuming similar proportional effects of renal impairment in adults and pediatric patients 6 years and older.]
eGFR 30 to 89 mL/min/1.73m | 4 mg
eGFR 15 to 29 mL/min/1.73m | Use is Not Recommended
eGFR <15 mL/min/1.73m^2 or requiring dialysis | Use is Not Recommended

Pediatric Patients weighing greater than 35 kg

The recommended dosage of Toviaz in pediatric patients with renal impairment weighing greater than 35 kg is described in Table 3 [see Use in Specific Populations (8.6)]. For administration instructions, see Dosage and Administration (2.6).

Table 3: Toviaz Recommended Dose in Pediatric Patients Aged 6 Years and Older Weighing Greater Than 35 kg With Renal Impairment (Administered Orally Once Daily)

Estimated GFR [Estimate GFR using a validated GFR estimating equation for the pediatric age range of the approved indication.] | Recommended Dose [Dosing was derived assuming similar proportional effects of renal impairment in adults and pediatric patients 6 years and older.]
eGFR 30 to 89 mL/min/1.73m [The recommended starting dosage of Toviaz is 4 mg orally once daily. After one week, increase to the recommended dosage of Toviaz 8 mg orally once daily.] | 8 mg
eGFR15 to 29 mL/min/1.73m | 4 mg
eGFR <15 mL/min/1.73m^2 or requiring dialysis | Use is Not Recommended

2.5 Toviaz Dosage Modifications Due to Strong CYP3A4 Inhibitors

Adult Patients with OAB

The maximum recommended dosage is Toviaz 4 mg orally once daily in adult patients taking strong CYP3A4 inhibitors [see Drug Interactions (7.2) and Clinical Pharmacology (12.3)]. For administration instructions, see Dosage and Administration (2.6).

Pediatric Patients with NDO

Pediatric Patients Weighing Greater than 25 kg and up to 35 kg

The use of Toviaz in pediatric patients weighing greater than 25 kg and up to 35 kg and taking strong CYP3A4 inhibitors is not recommended [see Drug Interactions (7.2) and Clinical Pharmacology (12.3)]. For administration instructions, see Dosage and Administration (2.6).

Pediatric Patients Weighing Greater than 35 kg

The maximum recommended dosage is Toviaz 4 mg orally once daily in pediatric patients weighing greater than 35 kg and taking strong CYP3A4 inhibitors [see Drug Interactions (7.2) and Clinical Pharmacology (12.3)]. For administration instructions, see Dosage and Administration (2.6).

2.6 Administration Instructions

Swallow Toviaz whole with liquid. Do not chew, divide, or crush. Take with or without food [see Clinical Pharmacology (12.3)].

3 DOSAGE FORMS AND STRENGTHS

Extended-release tablets:

- 4 mg, light blue, oval, biconvex, film-coated, and engraved with "FS" on one side.
- 8 mg, blue, oval, biconvex, film-coated, and engraved with "FT" on one side.

4 CONTRAINDICATIONS

Toviaz is contraindicated in patients with any of the following:

- known or suspected hypersensitivity to Toviaz or any of its ingredients, or to tolterodine tartrate tablets or tolterodine tartrate extended-release capsules [see Clinical Pharmacology (12.1)]. Reactions have included angioedema [see Warnings and Precautions (5.1)]
- urinary retention [see Warnings and Precautions (5.2)]
- gastric retention [see Warnings and Precautions (5.3)]
- uncontrolled narrow-angle glaucoma [see Warnings and Precautions (5.4)]

5 WARNINGS AND PRECAUTIONS

5.1 Angioedema

Angioedema of the face, lips, tongue, and/or larynx has been reported with Toviaz. In some cases, angioedema occurred after the first dose; however, cases have been reported to occur hours after the first dose or after multiple doses. Angioedema associated with upper airway swelling may be life-threatening.

Toviaz is contraindicated in patients with a known or suspected hypersensitivity to Toviaz or any of its ingredients [see Contraindications (4)]. If involvement of the tongue, hypopharynx, or larynx occurs, Toviaz should be promptly discontinued and appropriate therapy and/or measures to ensure a patent airway should be promptly provided.

5.2 Urinary Retention in Adult Patients With Bladder Outlet Obstruction

The use of Toviaz, like other antimuscarinic drugs, in patients with clinically significant bladder outlet obstruction, including patients with urinary retention, may result in further urinary retention and kidney injury. The use of Toviaz is not recommended in patients with clinically significant bladder outlet obstruction, and is contraindicated in patients with urinary retention [see Contraindications (4) and Adverse Reactions (6.1)].

5.3 Decreased Gastrointestinal Motility

Toviaz is associated with decreased gastric motility. Toviaz is contraindicated in patients with gastric retention [see Contraindications (4)]. The use of Toviaz is not recommended in patients with decreased gastrointestinal motility, such as those with severe constipation.

5.4 Worsening of Narrow-Angle Glaucoma

Toviaz can worsen controlled narrow-angle glaucoma. Toviaz is contraindicated in patients with uncontrolled narrow-angle glaucoma [see Contraindications (4)]. Toviaz should be used with caution in patients being treated for narrow-angle glaucoma.

5.5 Central Nervous System Effects

Toviaz is associated with anticholinergic central nervous system (CNS) adverse reactions [see Adverse Reactions (6.1)]. A variety of CNS anticholinergic effects have been reported, including headache, dizziness, and somnolence. Patients should be monitored for signs of anticholinergic CNS effects, particularly after beginning treatment or increasing the dose. Advise patients not to drive or operate heavy machinery until they know how Toviaz affects them. If a patient experiences anticholinergic CNS effects, Toviaz dose reduction or discontinuation should be considered.

5.6 Worsening of Myasthenia Gravis Symptoms

Toviaz should be used with caution in patients with myasthenia gravis due to the risk of worsening of symptoms of the disease.

6 ADVERSE REACTIONS

The following clinically significant adverse reactions are described elsewhere in labeling:

- Angioedema [see Warnings and Precautions (5.1)]
- Urinary Retention [see Warnings and Precautions (5.2)]
- Decreased Gastrointestinal Motility [see Warnings and Precautions (5.3)]

6.1 Clinical Trials Experience

Because clinical trials are conducted under widely varying conditions, adverse reaction rates observed in the clinical trials of a drug cannot be directly compared to rates in the clinical trials of another drug and may not reflect the rates observed in practice.

Adult Overactive Bladder (OAB)

The safety of Toviaz was evaluated in Phase 2 and 3 controlled trials in a total of 2859 patients with overactive bladder, of which 2288 were treated with Toviaz. Of this total, 782 received Toviaz 4 mg/day, and 785 received Toviaz 8 mg/day with treatment periods of 8- or 12-weeks. Approximately 80% of these patients had greater than 10-weeks of exposure to Toviaz in these trials.

A total of 1964 patients participated in two 12-week, Phase 3 efficacy and safety studies and subsequent open-label extension studies. In these two studies combined, 554 patients received Toviaz 4 mg/day and 566 patients received Toviaz 8 mg/day.

In Phase 2 and 3 placebo-controlled trials combined, the incidences of serious adverse events in patients receiving placebo, Toviaz 4 mg, and Toviaz 8 mg were 1.9%, 3.5%, and 2.9%, respectively. All serious adverse events were judged to be not related or unlikely to be related to study medication by the investigator, except for four patients receiving Toviaz who reported one serious adverse reaction each: angina, chest pain, gastroenteritis, and QT prolongation on ECG.

The most commonly reported adverse event in patients treated with Toviaz was dry mouth. The incidence of dry mouth was higher in those taking 8 mg/day (35%) and in those taking 4 mg/day (19%), as compared to placebo (7%). Dry mouth led to discontinuation in 0.4%, 0.4%, and 0.8% of patients receiving placebo, Toviaz 4 mg, and Toviaz 8 mg, respectively. For those patients who reported dry mouth, most had their first occurrence of the event within the first month of treatment.

The second most commonly reported adverse event was constipation. The incidence of constipation was 2% in those taking placebo, 4% in those taking 4 mg/day, and 6% in those taking 8 mg/day.

Table 4 lists adverse events, regardless of causality, that were reported in the combined Phase 3, randomized, placebo-controlled trials at an incidence greater than placebo and in 1% or more of patients treated with Toviaz 4 mg or 8 mg once daily for up to 12-weeks.

Table 4: Adverse Events With an Incidence Exceeding the Placebo Rate and Reported by ≥1% of Patients From Double-Blind, Placebo-Controlled Phase 3 Trials of 12-Weeks Treatment Duration
System organ class/Preferred term | Placebo N=554 % | Toviaz 4 mg/day N=554 % | Toviaz 8 mg/day N=566 %
Gastrointestinal disorders
Dry mouth | 7.0 | 18.8 | 34.6
Constipation | 2.0 | 4.2 | 6.0
Dyspepsia | 0.5 | 1.6 | 2.3
Nausea | 1.3 | 0.7 | 1.9
Abdominal pain upper | 0.5 | 1.1 | 0.5
Infections
Urinary tract infection | 3.1 | 3.2 | 4.2
Upper respiratory tract infection | 2.2 | 2.5 | 1.8
Eye disorders
Dry eyes | 0 | 1.4 | 3.7
Renal and urinary disorders
Dysuria | 0.7 | 1.3 | 1.6
Urinary retention | 0.2 | 1.1 | 1.4
Respiratory disorders
Cough | 0.5 | 1.6 | 0.9
Dry throat | 0.4 | 0.9 | 2.3
General disorders
Edema peripheral | 0.7 | 0.7 | 1.2
Musculoskeletal disorders
Back pain | 0.4 | 2.0 | 0.9
Psychiatric disorders
Insomnia | 0.5 | 1.3 | 0.4
Investigations
ALT increased | 0.9 | 0.5 | 1.2
GGT increased | 0.4 | 0.4 | 1.2
Skin disorders
Rash | 0.5 | 0.7 | 1.1
ALT = alanine aminotransferase; GGT = gamma glutamyltransferase

Patients also received Toviaz for up to three years in open-label extension phases of one Phase 2 and two Phase 3 controlled trials. In all open-label trials combined, 857, 701, 529, and 105 patients received Toviaz for at least 6 months, 1 year, 2 years, and 3 years, respectively. The adverse events observed during long-term, open-label studies were similar to those observed in the 12-week, placebo-controlled studies, and included dry mouth, constipation, dry eyes, dyspepsia, and abdominal pain. Similar to the controlled studies, most adverse events of dry mouth and constipation were mild to moderate in intensity. Serious adverse events, judged to be at least possibly related to study medication by the investigator and reported more than once during the open-label treatment period of up to 3 years, included urinary retention (3 cases), diverticulitis (3 cases), constipation (2 cases), irritable bowel syndrome (2 cases), and electrocardiogram QT corrected interval prolongation (2 cases).

Pediatric Neurogenic Detrusor Overactivity (NDO)

The safety of Toviaz was evaluated in a total of 131 pediatric patients with NDO. Patients received Toviaz 4 mg or Toviaz 8 mg orally once daily in two clinical trials (Studies 3 and 4).

Study 3 was a Phase 3 study in pediatric patients with NDO from 6 years to 17 years of age and weighing greater than 25 kg. This study consisted of a 12-week efficacy phase, in which 84 patients received Toviaz, followed by a 12-week safety extension phase, in which 103 patients received Toviaz. Of the 103 patients who received Toviaz in the safety extension phase, 67 continued Toviaz from the efficacy phase and 36 switched from an active comparator in the efficacy phase to Toviaz in the safety extension phase.

Study 4 (N=11) was an 8-week, Phase 2 pharmacokinetic (PK) and safety study in pediatric patients with NDO from 8 years to 17 years of age.

The most commonly reported adverse reactions in pediatric patients with NDO who received Toviaz 4 mg or 8 mg in Study 3 (≥2%) were diarrhea, UTI, dry mouth, constipation, abdominal pain, nausea, weight increased and headache.

Table 5 lists the adverse reactions reported at an incidence greater than or equal to 2% in either treatment group in the Study 3 efficacy phase.

Table 5: Adverse Reactions Reported in ≥2% of Patients With NDO Aged 6 Years to 17 Years in the 12-Week Efficacy Phase of Study 3
Preferred term | Toviaz 4 mg (N=42) % | Toviaz 8 mg (N=42) %
Diarrhea | 11.9 | 7.1
Urinary tract infection | 9.5 | 2.4
Dry mouth | 7.1 | 9.5
Constipation | 7.1 | 7.1
Abdominal pain [Includes abdominal pain and abdominal pain upper] | 7.1 | 4.8
Nausea | 4.8 | 2.4
Weight increased | 4.8 | 0
Headache | 4.8 | 7.1

Ophthalmological Adverse Reactions

Ophthalmological adverse reactions, including myopia, accommodation disorder and blurred vision, were reported in 8 of 131 (6.1%) pediatric patients with NDO who received Toviaz 4 mg or Toviaz 8 mg in Study 3 (both efficacy and safety extension phases) and Study 4. The ophthalmological adverse reactions did not result in discontinuation of Toviaz in any patient.

Increases in Heart Rate

Increases in heart rate were reported in pediatric patients with NDO who received Toviaz 4 mg and Toviaz 8 mg in Study 3. The mean heart data are described in Table 6.

Table 6: Mean Baseline and Mean Changes From Baseline in Heart Rate in Pediatric Patients Weighing Greater Than 25 kg in Study 3
Study visit | Mean heart rate in beats per minute [Heart rate expressed as the mean of the baseline measurement and the mean at each study visit and mean changes from baseline at each study visit by original treatment group in patients with complete follow-up at all study visits.] (mean change from baseline)
Study visit | Toviaz 4 mg | Toviaz 8 mg
Baseline | 88.6 | 84.2
Week 4 | 93.8 (+5.2) | 94.0 (+9.8)
Week 12 | 94.8 (+6.2) | 94.0 (+9.8)
Week 24 | 90.4 (+1.8) | 90.8 (+6.5)

The proportion of patients with heart rates greater than the 99th percentile for age also increased from baseline in patients who received Toviaz 4 mg and Toviaz 8 mg in Study 3. These data are described in Table 7.

Table 7: Proportion of Pediatric Patients With Heart Rate Greater Than the 99th Percentile for Age and Weighing Greater Than 25 kg in Study 3
Study visit | Proportion of patients with heart rate >99th percentile for age
Study visit | Toviaz 4 mg | Toviaz 8 mg
Baseline | 2.4% | 2.4%
Week 4 | 8.1% | 12.2%
Week 12 [Week 12 comprises patients who received Toviaz for 12 weeks after being originally randomized to Toviaz 4 mg and 8 mg and patients originally randomized to active comparator and subsequently transitioned to Toviaz 4 mg and 8 mg for 12 weeks.] | 7.5% | 11.5%
Week 24 | 3.3% | 2.7%

Increases from baseline in the proportion of patients with a heart rate greater than the 99th percentile for age were most pronounced in patients less than 12 years of age who received Toviaz 8 mg.

Increases in heart rate in patients who received Toviaz 4 mg and Toviaz 8 mg in Study 3 were not associated with clinical symptoms and did not result in discontinuation of therapy with Toviaz.

6.2 Postmarketing Experience

The following adverse reactions have been identified during post-approval use of Toviaz. Because these reactions are reported voluntarily from a population of uncertain size, it is not always possible to reliably estimate their frequency or establish a causal relationship to drug exposure.

Cardiac disorders: Palpitations

Central nervous system disorders: Dizziness, headache, somnolence

Eye disorders: Blurred vision

Gastrointestinal disorders: Hypoaesthesia oral

General disorders and administrative site conditions: Hypersensitivity reactions, including angioedema with airway obstruction, face edema

Psychiatric disorders: Confusional state

Skin and subcutaneous tissue disorders: Urticaria, pruritus

7 DRUG INTERACTIONS

7.1 Antimuscarinic Drugs

Coadministration of Toviaz with other antimuscarinic agents that produce dry mouth, constipation, urinary retention, and other anticholinergic pharmacological effects may increase the frequency and/or severity of such effects. Anticholinergic agents may potentially alter the absorption of some concomitantly administered drugs due to anticholinergic effects on gastrointestinal motility.

7.2 CYP3A4 Inhibitors

Doses of Toviaz greater than 4 mg are not recommended in adult patients taking strong CYP3A4 inhibitors, such as ketoconazole, itraconazole, and clarithromycin [see Dosage and Administration (2.5)]. The Toviaz dose in pediatric patients taking strong CYP3A4 inhibitors is recommended to be reduced to 4 mg once daily in patients >35 kg and is not recommended in patients weighing greater than 25 kg and up to 35 kg [see Dosage and Administration (2.5)].

In a study in adults, coadministration of the strong CYP3A4 inhibitor ketoconazole with fesoterodine led to approximately a doubling of the maximum concentration (Cmax) and area under the concentration versus time curve (AUC) of 5-hydroxymethyl tolterodine (5-HMT), the active metabolite of fesoterodine. Compared with CYP2D6 extensive metabolizers not taking ketoconazole, further increases in the exposure to 5-HMT were observed in subjects who were CYP2D6 poor metabolizers taking ketoconazole [see Clinical Pharmacology (12.3)].

There is no clinically relevant effect of moderate CYP3A4 inhibitors on the pharmacokinetics of fesoterodine. Following blockade of CYP3A4 by coadministration of the moderate CYP3A4 inhibitor fluconazole 200 mg twice a day for 2 days, the average (90% confidence interval) increase in Cmax and AUC of the active metabolite of fesoterodine was approximately 19% (11%–28%) and 27% (18%–36%) respectively. No dosing adjustments are recommended in the presence of moderate CYP3A4 inhibitors (e.g., erythromycin, fluconazole, diltiazem, verapamil and grapefruit juice).

The effect of weak CYP3A4 inhibitors (e.g. cimetidine) was not examined; it is not expected to be in excess of the effect of moderate inhibitors [see Clinical Pharmacology (12.3)].

7.3 CYP3A4 Inducers

No dosing adjustments are recommended in the presence of CYP3A4 inducers, such as rifampin and carbamazepine. Following induction of CYP3A4 by coadministration of rifampin 600 mg once a day, Cmax and AUC of the active metabolite of fesoterodine decreased by approximately 70% and 75%, respectively, after oral administration of Toviaz 8 mg. The terminal half-life of the active metabolite was not changed.

7.4 CYP2D6 Inhibitors

The interaction with CYP2D6 inhibitors was not tested clinically. In poor metabolizers for CYP2D6, representing a maximum CYP2D6 inhibition, Cmax and AUC of the active metabolite are increased 1.7- and 2-fold, respectively.

No dosing adjustments are recommended in the presence of CYP2D6 inhibitors.

7.5 Drugs Metabolized by Cytochrome P450

In vitro data indicate that at therapeutic concentrations, the active metabolite of fesoterodine does not have the potential to inhibit or induce Cytochrome P450 enzyme systems [see Clinical Pharmacology (12.3)].

7.6 Oral Contraceptives

In the presence of fesoterodine, there are no clinically significant changes in the plasma concentrations of combined oral contraceptives containing ethinyl estradiol and levonorgestrel [see Clinical Pharmacology (12.3)].

7.7 Warfarin

A clinical study has shown that fesoterodine 8 mg once daily has no significant effect on the pharmacokinetics or the anticoagulant activity (PT/INR) of warfarin 25 mg. Standard therapeutic monitoring for warfarin should be continued [see Clinical Pharmacology (12.3)].

7.8 Drug-Laboratory Test Interactions

Interactions between Toviaz and laboratory tests have not been studied.

8 USE IN SPECIFIC POPULATIONS

8.1 Pregnancy

Risk Summary

There are no available data with the use of Toviaz in pregnant women and adolescents to evaluate for a drug-associated risk of major birth defects, miscarriage or adverse maternal or fetal outcomes. In animal reproduction studies, oral administration of fesoterodine to pregnant mice and rabbits during organogenesis resulted in fetotoxicity at maternal exposures that were 6 and 3 times respectively the maximum recommended human dose (MRHD) of 8 mg/day, based on AUC (see Data). The background risk of major birth defects and miscarriage for the indicated population are unknown. However, in the U.S. general population, the estimated background risk of major birth defects and miscarriage in clinically recognized pregnancies is 2–4% and 15–20%, respectively.

Data

Animal Data

No dose-related teratogenicity was observed in reproduction studies performed in mice and rabbits. In mice at 6 to 27 times the expected exposure at the maximum recommended human dose (MRHD) of 8 mg based on AUC (75 mg/kg/day, oral), increased resorptions and decreased live fetuses were observed. One fetus with cleft palate was observed at each dose (15, 45, and 75 mg/kg/day), at an incidence within the background historical range. In rabbits treated at 3 to 11 times the MRHD (27 mg/kg/day, oral), incompletely ossified sternebrae (retardation of bone development) and reduced survival were observed in fetuses. In rabbits at 9 to 11 times the MRHD (4.5 mg/kg/day, subcutaneous), maternal toxicity and incompletely ossified sternebrae were observed in fetuses (at an incidence within the background historical range). In rabbits at 3 times the MRHD (1.5 mg/kg/day, subcutaneous), decreased maternal food consumption in the absence of any fetal effects was observed. Oral administration of 30 mg/kg/day fesoterodine to mice in a pre- and post-natal development study resulted in decreased body weight of the dams and delayed ear opening of the pups. No effects were noted on mating and reproduction of the F1 dams or on the F2 offspring.

8.2 Lactation

Risk Summary

There is no information on the presence of fesoterodine in human milk, the effects on the breastfed child, or the effects on milk production. The developmental and health benefits of breastfeeding should be considered along with the mother's clinical need for Toviaz and any potential adverse effects on the breastfed child from Toviaz or from the underlying maternal condition.

8.4 Pediatric Use

The safety and effectiveness of Toviaz have been established for the treatment of neurogenic detrusor overactivity (NDO) in pediatric patients aged 6 years and older and weighing greater than 25 kg. The information on this use is discussed throughout labeling. Use of Toviaz for treatment of NDO is supported by evidence from a randomized, open-label trial with an initial 12-week efficacy phase followed by a 12-week safety extension phase in pediatric patients from 6 years to 17 years of age (Study 3) [see Adverse Reactions (6.1) and Clinical Studies (14.2)]. Study results demonstrated that treatment with Toviaz 4 mg and 8 mg daily resulted in improvements from baseline to Week 12 in maximum cystometric bladder capacity (MCBC) for patients weighing greater than 25 kg [see Clinical Studies (14.2) and Clinical Pharmacology (12.3)]. The most commonly reported adverse reactions in patients who received Toviaz 4 mg or 8 mg in Study 3 (≥2%) were diarrhea, UTI, dry mouth, constipation, abdominal pain, nausea, weight increase and headache [see Adverse Reactions (6.1)]. Mean increases from baseline in heart rate were reported with both the 4 mg and 8 mg daily doses of Toviaz, with larger mean increases reported in pediatric patients who received the 8 mg daily dose [see Adverse Reactions (6.1)].

The safety and effectiveness of Toviaz have not been established in pediatric patients younger than 6 years of age or weighing 25 kg or less.

8.5 Geriatric Use

No dose adjustment is recommended for the elderly. The pharmacokinetics of fesoterodine are not significantly influenced by age.

Of the 1,567 patients who received Toviaz 4 mg or 8 mg orally once daily in Phase 2 and 3, placebo-controlled, efficacy and safety studies for OAB, 515 (33%) were 65 years of age or older, and 140 (9%) were 75 years of age or older. No overall difference in effectiveness was observed between patients younger than 65 years of age and those 65 years of age or older in these studies. However, the incidence of antimuscarinic adverse reactions, including dry mouth, constipation, dyspepsia, increase in residual urine, dizziness (8 mg only) and urinary tract infection, was higher in patients 75 years of age and older as compared to younger patients [see Clinical Studies (14.1) and Adverse Reactions (6)].

8.6 Renal Impairment

In adult patients with severe renal impairment (CLCR <30 mL/min), Cmax and AUC are increased 2.0- and 2.3-fold, respectively. Doses of Toviaz greater than 4 mg are not recommended in adult patients with severe renal impairment. In patients with mild or moderate renal impairment (CLCR ranging from 30–80 mL/min), Cmax and AUC of the active metabolite are increased up to 1.5- and 1.8-fold, respectively, as compared to healthy subjects. No dose adjustment is recommended in patients with mild or moderate renal impairment [see Clinical Pharmacology (12.3) and Dosage and Administration (2.2, 2.3)].

The recommended dosage of Toviaz in pediatric patients weighing greater than 25 kg and up to 35 kg with mild-to-moderate renal impairment (eGFR 30 to 89 mL/min/1.73m^2) is 4 mg once daily and Toviaz is not recommend in those with severe renal impairment (eGFR 15 to 29 mL/min/1.73m^2). In pediatric patients weighing greater than 35 kg with mild-to-moderate renal impairment (eGFR 30 to 89 mL/min/1.73m^2), the recommended starting dosage of Toviaz is 4 mg orally once daily, with increase to the recommended dosage of Toviaz 8 mg orally once daily, and in those with severe renal impairment (eGFR 15 to 29 mL/min/1.73m^2) the recommended dose is 4 mg once daily [see Dosage and Administration (2.2, 2.4)].

8.7 Hepatic Impairment

Patients with severe hepatic impairment (Child-Pugh C) have not been studied; therefore Toviaz is not recommended for use in these patients. In patients with moderate (Child-Pugh B) hepatic impairment, Cmax and AUC of the active metabolite are increased 1.4- and 2.1-fold, respectively, as compared to healthy subjects. No dose adjustment is recommended in patients with mild or moderate hepatic impairment [see Clinical Pharmacology (12.3)].

10 OVERDOSAGE

Overdosage with Toviaz can result in severe anticholinergic effects. Treatment should be symptomatic and supportive. In the event of overdosage, ECG monitoring is recommended.

11 DESCRIPTION

Toviaz contains fesoterodine fumarate and is an extended-release tablet. Fesoterodine is rapidly de-esterified to its active metabolite (R)-2-(3-diisopropylamino-1-phenylpropyl)-4-hydroxymethyl-phenol, or 5-hydroxymethyl tolterodine, which is a muscarinic receptor antagonist.

Chemically, fesoterodine fumarate is designated as isobutyric acid 2-((R)-3-diisopropylammonium-1-phenylpropyl)-4-(hydroxymethyl) phenyl ester hydrogen fumarate. The empirical formula is C30H41NO7 and its molecular weight is 527.66. The structural formula is:

The asterisk (*) indicates the chiral carbon.

Fesoterodine fumarate is a white to off-white powder, which is freely soluble in water. Each Toviaz extended-release tablet contains either 4 mg or 8 mg of fesoterodine fumarate and the following inactive ingredients: glyceryl behenate, hypromellose, indigo carmine aluminum lake, lactose monohydrate, soya lecithin, microcrystalline cellulose, polyethylene glycol, polyvinyl alcohol, talc, titanium dioxide, and xylitol.

12 CLINICAL PHARMACOLOGY

12.1 Mechanism of Action

Fesoterodine is a competitive muscarinic receptor antagonist. After oral administration, fesoterodine is rapidly and extensively hydrolyzed by nonspecific esterases to its active metabolite, 5-hydroxymethyl tolterodine, which is responsible for the antimuscarinic activity of fesoterodine.

Muscarinic receptors play a role in contractions of urinary bladder smooth muscle. Inhibition of these receptors in the bladder is presumed to be the mechanism by which fesoterodine produces its effects.

12.2 Pharmacodynamics

In a urodynamic study involving patients with involuntary detrusor contractions, the effects after the administration of fesoterodine on the volume at first detrusor contraction and bladder capacity were assessed. Administration of fesoterodine increased the volume at first detrusor contraction and bladder capacity in a dose-dependent manner. These findings are consistent with an antimuscarinic effect on the bladder.

Cardiac Electrophysiology

The effect of fesoterodine 4 mg and 28 mg on the QT interval was evaluated in a double-blind, randomized, placebo- and positive-controlled (moxifloxacin 400 mg once a day) parallel trial with once-daily treatment over a period of 3 days in 261 male and female subjects aged 44 to 65 years. Electrocardiographic parameters were measured over a 24-hour period at pre-dose, after the first administration, and after the third administration of study medication. Fesoterodine 28 mg was chosen because this dose, when administered to CYP2D6 extensive metabolizers, results in an exposure to the active metabolite that is similar to the exposure in a CYP2D6 poor metabolizer receiving fesoterodine 8 mg together with CYP3A4 blockade. Corrected QT intervals (QTc) were calculated using Fridericia's correction and a linear individual correction method. Analyses of 24-hour average QTc, time-matched baseline-corrected QTc, and time-matched placebo-subtracted QTc intervals indicate that fesoterodine at doses of 4 and 28 mg/day did not prolong the QT interval. The sensitivity of the study was confirmed by positive QTc prolongation by moxifloxacin.

In this study, conducted in subjects aged 44 to 65 years, Toviaz was associated with an increase in heart rate that correlates with increasing dose. When compared to placebo, the mean increase in heart rate associated with fesoterodine 4 mg/day and fesoterodine 28 mg/day was 3 beats/minute and 11 beats/minute, respectively.

In the two, phase 3, placebo-controlled studies in adult in patients with overactive bladder, the mean increases in heart rate compared to placebo were 3–4 beats/minute in the fesoterodine 4 mg/day group and 3–5 beats/minute in the fesoterodine 8 mg/day group.

12.3 Pharmacokinetics

Absorption

After oral administration, fesoterodine is well absorbed. Due to rapid and extensive hydrolysis by nonspecific esterases to its active metabolite 5-hydroxymethyl tolterodine, fesoterodine cannot be detected in plasma. Bioavailability of the active metabolite is 52%. After single or multiple-dose oral administration of fesoterodine in doses from 4 mg to 28 mg, plasma concentrations of the active metabolite are proportional to the dose. Maximum plasma levels are reached after approximately 5 hours. No accumulation occurs after multiple-dose administration.

A Summary of pharmacokinetic parameters for the active metabolite after a single dose of Toviaz 4 mg and 8 mg in extensive and poor metabolizers of CYP2D6 is provided in Table 8.

Table 8: Summary of Geometric Mean [CV] Pharmacokinetic Parameters for the Active Metabolite After a Single Dose of Toviaz 4 mg and 8 mg in Extensive and Poor CYP2D6 Metabolizers
 | Toviaz 4 mg |  | Toviaz 8 mg
Parameter | EM (N=16) | PM (N=8) | EM (N=16) | PM (N=8)
Cmax (ng/mL) | 1.89 [43%] | 3.45 [54%] | 3.98 [28%] | 6.90 [39%]
AUC0–tz (ng*h/mL) | 21.2 [38%] | 40.5 [31%] | 45.3 [32%] | 88.7 [36%]
tmax (h) [Data presented as median (range)] | 5 [2–6] | 5 [5–6] | 5 [3–6] | 5 [5–6]
t½ (h) | 7.31 [27%] | 7.31 [30%] | 8.59 [41%] | 7.66 [21%]
EM = extensive CYP2D6 metabolizer, PM = poor CYP2D6 metabolizer, CV = coefficient of variation; Cmax = maximum plasma concentration, AUC0–tz = area under the concentration time curve from zero up to the last measurable plasma concentration, tmax = time to reach Cmax, t½ = terminal half-life

Effect of Food

There is no clinically relevant effect of food on the pharmacokinetics of fesoterodine. In a study of the effects of food on the pharmacokinetics of fesoterodine in 16 healthy male volunteers, concomitant food intake increased the active metabolite of fesoterodine AUC by approximately 19% and Cmax by 18% [see Dosage and Administration (2.1)].

Distribution

Plasma protein binding of the active metabolite is low (approximately 50%) and is primarily bound to albumin and alpha-1-acid glycoprotein. The mean steady-state volume of distribution following intravenous infusion of the active metabolite is 169 L.

Metabolism

After oral administration, fesoterodine is rapidly and extensively hydrolyzed to its active metabolite. The active metabolite is further metabolized in the liver to its carboxy, carboxy-N-desisopropyl, and N-desisopropyl metabolites via two major pathways involving CYP2D6 and CYP3A4. None of these metabolites contribute significantly to the antimuscarinic activity of fesoterodine.

Variability in CYP2D6 Metabolism

A subset of individuals (approximately 7% of Caucasians and approximately 2% of African Americans) are poor metabolizers for CYP2D6. Cmax and AUC of the active metabolite are increased 1.7- and 2-fold, respectively, in CYP2D6 poor metabolizers, as compared to extensive metabolizers.

Excretion

Hepatic metabolism and renal excretion contribute significantly to the elimination of the active metabolite. After oral administration of fesoterodine, approximately 70% of the administered dose was recovered in urine as the active metabolite (16%), carboxy metabolite (34%), carboxy-N-desisopropyl metabolite (18%), or N-desisopropyl metabolite (1%), and a smaller amount (7%) was recovered in feces.

The terminal half-life of the active metabolite is approximately 4 hours following an intravenous administration. The apparent terminal half-life following oral administration is approximately 7 hours.

Pharmacokinetics in Specific Populations

Geriatric Patients

Following a single 8 mg oral dose of fesoterodine, the mean (±SD) AUC and Cmax for the active metabolite 5-hydroxymethyl tolterodine in 12 elderly men (mean age 67 years) were 51.8 ± 26.1 h*ng/mL and 3.8 ± 1.7 ng/mL, respectively. In the same study, the mean (±SD) AUC and Cmax in 12 young men (mean age 30 years) were 52.0 ± 31.5 h*ng/mL and 4.1 ± 2.1 ng/mL, respectively. The pharmacokinetics of fesoterodine were not significantly influenced by age [see Use in Specific Populations (8.5)].

Pediatric Patients

In pediatric patients, from 6 years to 17 years of age with NDO weighing 35 kg with CYP2D6 extensive metabolizer status receiving Toviaz tablets, the mean values of apparent oral clearance, volume of distribution and absorption rate constant of 5-HMT are estimated to be approximately 72 L/h, 68 L and 0.09 h-1, respectively. The Tmax and half-life of 5-HMT are estimated to be approximately 2.55 h and 7.73 h, respectively. Like adults, the 5-HMT exposures in CYP2D6 poor metabolizers was estimated to be approximately 2-fold higher compared with extensive metabolizers.

The post-hoc estimates of steady-state exposures of 5-HMT in NDO patients weighing greater than 25 kg following Toviaz 4 mg and 8 mg tablets once daily are summarized in Table 9.

Table 9: Summary of Geometric Mean [%CV] Pharmacokinetic Parameters for the Active Metabolite After Steady-State Dosing of Fesoterodine in Pediatric Patients With NDO, Ages 6–17 Years Weighing Greater Than 25 kg
Dosage | N | Cmax,ss (ng/mL) | AUCtau,ss (ng*h/mL)
4 mg once daily | 32 | 4.88 (48.2) | 59.1 (51.7)
8 mg once daily | 39 | 8.47 (41.6) | 103 (46.2)
CV = coefficient of variation; Cmax,ss = steady-state maximum plasma concentration, AUCtau,ss = steady-state area under the concentration time curve over the 24-hour dosing interval, N = number of patients with PK data

Gender

Following a single 8 mg oral dose of fesoterodine, the mean (±SD) AUC and Cmax for the active metabolite 5-hydroxymethyl tolterodine in 12 elderly men (mean age 67 years) were 51.8 ± 26.1 h*ng/mL and 3.8 ± 1.7 ng/mL, respectively. In the same study, the mean (±SD) AUC and Cmax in 12 elderly women (mean age 68 years) were 56.0 ± 28.8 h*ng/mL and 4.6 ± 2.3 ng/mL, respectively. The pharmacokinetics of fesoterodine were not significantly influenced by gender.

Race

The effects of Caucasian or Black race on the pharmacokinetics of fesoterodine were examined in a study of 12 Caucasian and 12 Black African young male volunteers. Each subject received a single oral dose of 8 mg fesoterodine. The mean (±SD) AUC and Cmax for the active metabolite 5-hydroxymethyl tolterodine in Caucasian males were 73.0 ± 27.8 h*ng/mL and 6.1 ± 2.7 ng/mL, respectively. The mean (±SD) AUC and Cmax in Black males were 65.8 ± 23.2 h*ng/mL and 5.5 ± 1.9 ng/mL, respectively. The pharmacokinetics of fesoterodine were not significantly influenced by race.

Renal Impairment

In patients with mild or moderate renal impairment (CLCR ranging from 30–80 mL/min), Cmax and AUC of the active metabolite are increased up to 1.5- and 1.8-fold, respectively, as compared to healthy subjects. In patients with severe renal impairment (CLCR <30 mL/min), Cmax and AUC are increased 2.0- and 2.3-fold, respectively [see Use in Specific Populations (8.6) and Dosage and Administration (2.2, 2.3)].

Hepatic Impairment

In patients with moderate (Child-Pugh B) hepatic impairment, Cmax and AUC of the active metabolite are increased 1.4- and 2.1-fold, respectively, as compared to healthy subjects.

Subjects with severe hepatic impairment (Child-Pugh C) have not been studied [see Use in Specific Populations (8.7)].

Drug-Drug Interactions

Drugs Metabolized by Cytochrome P450

At therapeutic concentrations, the active metabolite of fesoterodine does not inhibit CYP1A2, 2B6, 2C8, 2C9, 2C19, 2D6, 2E1, or 3A4, or induce CYP1A2, 2B6, 2C9, 2C19, or 3A4 in vitro [see Drug Interactions (7.5)].

CYP3A4 Inhibitors

Following blockade of CYP3A4 by coadministration of the strong CYP3A4 inhibitor ketoconazole 200 mg twice a day for 5 days, Cmax and AUC of the active metabolite of fesoterodine increased 2.0- and 2.3-fold, respectively, after oral administration of Toviaz 8 mg to CYP2D6 extensive metabolizers. In CYP2D6 poor metabolizers, Cmax and AUC of the active metabolite of fesoterodine increased 2.1- and 2.5-fold, respectively, during coadministration of ketoconazole 200 mg twice a day for 5 days. Cmax and AUC were 4.5- and 5.7-fold higher, respectively, in subjects who were CYP2D6 poor metabolizers and taking ketoconazole compared to subjects who were CYP2D6 extensive metabolizers and not taking ketoconazole. In a separate study coadministering fesoterodine with ketoconazole 200 mg once a day for 5 days, the Cmax and AUC values of the active metabolite of fesoterodine were increased 2.2-fold in CYP2D6 extensive metabolizers and 1.5- and 1.9-fold, respectively, in CYP2D6 poor metabolizers. Cmax and AUC were 3.4- and 4.2-fold higher, respectively, in subjects who were CYP2D6 poor metabolizers and taking ketoconazole compared to subjects who were CYP2D6 extensive metabolizers and not taking ketoconazole.

There is no clinically relevant effect of moderate CYP3A4 inhibitors on the pharmacokinetics of fesoterodine. In a drug-drug interaction study evaluating the coadministration of the moderate CYP3A4 inhibitor fluconazole 200 mg twice a day for 2 days, a single 8 mg dose of fesoterodine was administered 1 hour following the first dose of fluconazole on day 1 of the study. The average (90% confidence interval) for the increase in Cmax and AUC of the active metabolite of fesoterodine was approximately 19% (11% – 28%) and 27% (18% – 36%) respectively.

The effect of weak CYP3A4 inhibitors (e.g. cimetidine) was not examined; it is not expected to be in excess of the effect of moderate inhibitors [see Drug Interactions (7.2) and Dosage and Administration (2.2, 2.3)].

CYP3A4 Inducers

Following induction of CYP3A4 by coadministration of rifampicin 600 mg once a day, Cmax and AUC of the active metabolite of fesoterodine decreased by approximately 70% and 75%, respectively, after oral administration of Toviaz 8 mg. The terminal half-life of the active metabolite was not changed.

Induction of CYP3A4 may lead to reduced plasma levels. No dosing adjustments are recommended in the presence of CYP3A4 inducers [see Drug Interactions (7.3)].

CYP2D6 Inhibitors

The interaction with CYP2D6 inhibitors was not studied. In poor metabolizers for CYP2D6, representing a maximum CYP2D6 inhibition, Cmax and AUC of the active metabolite are increased 1.7- and 2-fold, respectively [see Drug Interactions (7.4)].

Oral Contraceptives

Thirty healthy female subjects taking an oral contraceptive containing 0.03 mg ethinyl estradiol and 0.15 mg levonorgestrel were evaluated in a 2-period cross-over study. Each subject was randomized to receive concomitant administration of either placebo or fesoterodine 8 mg once daily on days 1 – 14 of hormone cycle for 2 consecutive cycles. Pharmacokinetics of ethinyl estradiol and levonorgestrel were assessed on day 13 of each cycle. Fesoterodine increased the AUC and Cmax of ethinyl estradiol by 1 – 3% and decreased the AUC and Cmax of levonorgestrel by 11 – 13% [see Drug Interactions (7.6)].

Warfarin

In a cross-over study in 14 healthy male volunteers (18–55 years), a single oral dose of warfarin 25 mg was given either alone or on day 3 of once daily dosing for 9 days with fesoterodine 8 mg. Compared to warfarin alone dosing, the Cmax and AUC of S-warfarin were lower by ~ 4 %, while the Cmax and AUC of R-warfarin were lower by approximately 8 % and 6% for the coadministration, suggesting absence of a significant pharmacokinetic interaction.

There were no statistically significant changes in the measured pharmacodynamic parameters for anticoagulant activity of warfarin (INRmax, AUCINR), with only a small decrease noted in INRmax of ~ 3 % with the co-administration relative to warfarin alone. INR versus time profiles across individual subjects in the study suggested some differences following co-administration with fesoterodine, although there was no definite trend with regard to the changes noted [see Drug Interactions (7.7)].

13 NONCLINICAL TOXICOLOGY

13.1 Carcinogenesis, Mutagenesis, Impairment of Fertility

Carcinogenicity

No evidence of drug-related carcinogenicity was found in 24-month studies with oral administration to mice and rats. The highest tolerated doses in mice (females 45 to 60 mg/kg/day, males 30 to 45 mg/kg/day) correspond to 11 to 19 times (females) and 4 to 9 times (males) the estimated human AUC values reached with fesoterodine 8 mg, which is the Maximum Recommended Human Dose (MRHD). In rats, the highest tolerated dose (45 to 60 mg/kg/day) corresponds to 3 to 8 times (females) and 3 to 14 times (males) the estimated human AUC at the MRHD.

Mutagenesis

Fesoterodine was not mutagenic or genotoxic in vitro (Ames tests, chromosome aberration tests) or in vivo (mouse micronucleus test).

Impairment of Fertility

Fesoterodine had no effect on male reproductive function or fertility at doses up to 45 mg/kg/day in mice. At 45 mg/kg/day, a lower number of corpora lutea, implantation sites and viable fetuses was observed in female mice administered fesoterodine for 2-weeks prior to mating and continuing through day 7 of gestation. The maternal No-Observed-Effect Level (NOEL) and the NOEL for effects on reproduction and early embryonic development were both 15 mg/kg/day. At the NOEL, the systemic exposure, based on AUC, was 0.6 to 1.5 times higher in mice than in humans at the MRHD, whereas based on peak plasma concentrations, the exposure in mice was 5 to 9 times higher.

14 CLINICAL STUDIES

14.1 Adult Overactive Bladder

The efficacy of Toviaz extended-release tablets was evaluated in two, Phase 3, randomized, double-blind, placebo-controlled, 12-week studies for the treatment of overactive bladder with symptoms of urge urinary incontinence, urgency, and urinary frequency. Entry criteria required that patients have symptoms of overactive bladder for ≥6-months duration, at least 8 micturitions per day, and at least 6 urinary urgency episodes or 3 urge incontinence episodes per 3-day diary period. Patients were randomized to a fixed dose of Toviaz 4 or 8 mg/day or placebo. In one of these studies, 290 patients were randomized to an active control arm (an oral antimuscarinic agent). For the combined studies, a total of 554 patients received placebo, 554 patients received Toviaz 4 mg/day, and 566 patients received Toviaz 8 mg/day. The majority of patients were Caucasian (91%) and female (79%) with a mean age of 58 years (range 19–91 years).

The primary efficacy endpoints were the mean change in the number of urge urinary incontinence episodes per 24 hours and the mean change in the number of micturitions (frequency) per 24 hours. An important secondary endpoint was the mean change in the voided volume per micturition.

Results for the primary endpoints and for mean change in voided volume per micturition from the two 12-week clinical studies of Toviaz are reported in Table 10.

Table 10: Mean Baseline and Change From Baseline to Week 12 for Urge Urinary Incontinence Episodes, Number of Micturitions, and Volume Voided per Micturition
 | Study 1 |  |  | Study 2
Parameter | Placebo N=279 | Toviaz 4mg/day N=265 | Toviaz 8mg/day N=276 | Placebo N=266 | Toviaz 4mg/day N=267 | Toviaz 8mg/day N=267
Number of urge incontinence episodes per 24 hours [Only those patients who were urge incontinent at baseline were included for the analysis of number of urge incontinence episodes per 24 hours: In Study 1, the number of these patients was 211, 199, and 223 in the placebo, Toviaz 4 mg/day and Toviaz 8 mg/day groups, respectively. In Study 2, the number of these patients was 205, 228, and 218, respectively.]
Baseline | 3.7 | 3.8 | 3.7 | 3.7 | 3.9 | 3.9
Change from baseline | -1.20 | -2.06 | -2.27 | -1.00 | -1.77 | -2.42
p-value vs. placebo | - | 0.001 | <0.001 | - | <0.003 | <0.001
Number of micturitions per 24 hours
Baseline | 12.0 | 11.6 | 11.9 | 12.2 | 12.9 | 12.0
Change from baseline | -1.02 | -1.74 | -1.94 | -1.02 | -1.86 | -1.94
p-value vs. placebo | - | <0.001 | <0.001 | - | 0.032 | <0.001
Voided volume per micturition (mL)
Baseline | 150 | 160 | 154 | 159 | 152 | 156
Change from baseline | 10 | 27 | 33 | 8 | 17 | 33
p-value vs. placebo | - | <0.001 | <0.001 | - | 0.150 | <0.001
vs. = versus

Figures 1–4: The following figures show change from baseline over time in number of micturitions and urge urinary incontinence episodes per 24 h in the two studies.

A reduction in number of urge urinary incontinence episodes per 24 hours was observed for both doses as compared to placebo as early as two weeks after starting Toviaz therapy.

14.2 Pediatric Neurogenic Detrusor Overactivity

The efficacy of Toviaz was evaluated in Study 3 (NCT01557244), a Phase 3, randomized, open-label study consisting of a 12-week efficacy phase followed by a 12-week safety extension phase in pediatric patients from 6 years to 17 years of age. Two cohorts were studied. Cohort 1 (patients weighing greater than 25 kg) received a fixed dose of Toviaz 4 mg or Toviaz 8 mg tablets orally once daily, or once daily. In the safety extension phase, patients randomized to the active comparator were switched to Toviaz 4 mg or Toviaz 8 mg once daily. For study inclusion, patients were required to have stable neurological disease and clinically or urodynamically-demonstrated NDO. Cohort 2 patients weighing less than 25 kg received an investigational fesoterodine formulation.

During the 12-week efficacy phase, 124 patients (69 males and 55 females) were randomized to receive Toviaz 4 mg (N=42), Toviaz 8 mg (N=42), or active comparator (N=40) orally once daily. The majority of patients were Caucasian (52%) or Asian (44%) with a mean age of 11 years (range 6 years to 17 years) and a mean weight of 42.8 kg (range 25.1 to 96.0 kg).

Primary Endpoint

The primary efficacy endpoint was the mean change from baseline in maximum cystometric bladder capacity (MCBC) at Week 12.

Treatment with Toviaz 4 mg or 8 mg daily resulted in improvements from baseline to Week 12 in the primary efficacy endpoint, MCBC, for pediatric patients, with numerically higher changes from baseline for Toviaz 8 mg daily than for Toviaz 4 mg daily.

Results for the primary endpoint MCBC are reported in Table 11.

Table 11: Mean Baseline and Change From Baseline to Week 12 for Maximum Cystometric Bladder Capacity (mL) in Pediatric NDO Patients Receiving Toviaz 4 mg or Toviaz 8 mg and Weighing More Than 25 kg in Study 3
 | Toviaz 4 mg | Toviaz 8 mg
N | 41 | 41
Baseline | 195.1 | 173.3
Change from baseline; (95% CI) [Least squares mean change and 95% CI are based on an analysis of covariance model with terms for treatment group, baseline maximum cystometric bladder capacity and baseline weight. Last observation carried forward/baseline observation carried forward was used for imputing missing values at Week 12.] | 58.1; (28.8, 87.4) | 83.4; (54.2, 112.5)
CI = confidence interval
Baseline is defined as the last available measurement prior to the start of treatment.
N is the number of patients who took at least one dose and provided a valid value for MCBC at baseline.

Secondary Endpoints

Results for other urodynamic secondary efficacy endpoints and selected secondary efficacy endpoints derived from patient urinary diaries are reported in Tables 12 and 13, respectively.

Table 12: Summary of Baseline and Change From Baseline to Week 12 in Secondary Urodynamic Endpoints in Pediatric NDO Patients Weighing Greater Than 25 kg in Study 3
 | Toviaz 4 mg | Toviaz 8 mg
Detrusor pressure at maximum bladder capacity (cmH2O)
N | 40 | 41
Baseline | 26.5 | 27.2
Change from Baseline (95% CI) [Least squares mean change and 95% CI are based on an analysis of covariance model with terms for treatment group, baseline (for the endpoint being analyzed) and baseline weight. Last observation carried forward/baseline observation carried forward was used for imputing missing values at Week 12.] | -2.9 (-7.6, 1.9) | -1.6 (-6.3, 3.1)
Number and percentage of patients with IDC at Baseline but not at Week 12 (n (%))
N | 41 | 41
n (%) | 9 (22.0) | 18 (43.9)
Bladder volume at first IDC (mL)
N | 26 | 36
Baseline | 88.6 | 88.5
Change from Baseline (95% CI) | 30.5 (2.4, 58.6) | 26.1 (2.2, 49.9)
Bladder compliance (mL/cmH20)
N | 40 | 40
Baseline | 13.8 | 10.1
Change from Baseline (95% CI) | 6.4 (-0.5, 13.3) | 5.4 (-1.5, 12.3)
CI = confidence interval; IDC = involuntary detrusor contractions
Baseline is defined as the last available measurement prior to the start of treatment.
N is the number of patients who took at least one dose and provided valid endpoint data at baseline .

Table 13: Mean Baseline and Change From Baseline to Week 12 in Selected Secondary Bladder-Diary Endpoints in Pediatric NDO Patients Weighing Greater Than 25 kg in Study 3
 | Toviaz 4 mg | Toviaz 8 mg
Number of incontinence episodes per 24 hours [Only patients with >0 incontinence episodes at baseline are included.]
N | 33 | 33
Baseline | 2.8 | 2.7
Change from Baseline (95% CI) [Least squares mean change and 95% CI are based on an analysis of covariance model with terms for treatment group, baseline (for the endpoint being analyzed) and baseline weight. Last observation carried forward/baseline observation carried forward was used for imputing missing values at Week 12.] | -0.5 (-0.9, 0.0) | -0.9 (-1.4, -0.4)
Maximum catheterized urine volume per 24 hours (mL)
N | 36 | 32
Baseline | 222.5 | 164.7
Change from Baseline (95% CI) | 31.6 (-9.3, 72.6) | 51.0 (8.1, 93.8)
CI = confidence interval
Baseline is defined as the last available measurement prior to the start of treatment.
N is the number of patients who took at least one dose and provided valid endpoint data at baseline.

16 HOW SUPPLIED/STORAGE AND HANDLING

Toviaz (fesoterodine fumarate) extended-release tablets 4 mg are light blue, oval, biconvex, film-coated, and engraved with "FS" on one side. They are supplied as follows:

Bottles of 30 | NDC 0069-0242-30

Toviaz (fesoterodine fumarate) extended-release tablets 8 mg are blue, oval, biconvex, film-coated, and engraved with "FT" on one side. They are supplied as follows:

Bottles of 30 | NDC 0069-0244-30

STORAGE AND HANDLING

Store at 20° to 25°C (68° to 77°F); excursions permitted between 15° to 30°C (59° to 86°F) [see USP Controlled Room Temperature]. Protect from moisture.

17 PATIENT COUNSELING INFORMATION

Advise the patient to read the FDA-Approved Patient Labeling (Patient Information).

Angioedema

Inform patients and/or their caregivers that Toviaz may cause angioedema, which could result in life-threatening airway obstruction. Advise patients and/or their caregivers to promptly discontinue Toviaz and seek immediate medical attention if they experience edema of the lips, tongue or laryngopharynx, or difficulty breathing.

Antimuscarinic Effects

Inform patients that Toviaz, like other antimuscarinic agents, may produce clinically significant adverse effects related to antimuscarinic pharmacological activity including constipation and urinary retention. Toviaz, like other antimuscarinics, may be associated with blurred vision, therefore, patients should be advised to exercise caution in decisions to engage in potentially dangerous activities until the drug's effects on the patient have been determined. Heat prostration (due to decreased sweating) can occur when Toviaz, like other antimuscarinic drugs, is used in a hot environment.

Alcohol

Patients should also be informed that alcohol may enhance the drowsiness caused by Toviaz, like other anticholinergic agents.

This product's labeling may have been updated. For the most recent prescribing information, please visit www.pfizer.com.

LAB-0381-19.0

Patient Information
TOVIAZ® (TOH-vee-as)
(fesoterodine fumarate)
extended-release tablets, for oral use

Read the Patient Information that comes with TOVIAZ before you start taking it and each time you get a refill. There may be new information. This leaflet does not take the place of talking with your healthcare provider about your medical condition or your treatment.

What is TOVIAZ?
TOVIAZ is a prescription medicine used:

- in adults to treat symptoms of a condition called overactive bladder (OAB), including urge urinary incontinence (leaking or wetting accidents due to a strong need to urinate), urinary urgency (having a strong need to urinate right away), or urinary frequency (having to urinate too often).
- in children 6 years of age and older with a body weight greater than 55 pounds (25 kg) to treat neurogenic detrusor overactivity (NDO). TOVIAZ is used to increase the amount of urine your bladder can hold and reduce urine leakage.

It is not known if TOVIAZ is safe and effective in children younger than 6 years of age or with a body weight 55 pounds (25-kg) or less.

Who should not take TOVIAZ?
Do not take TOVIAZ if you:

- are allergic to TOVIAZ or any of its ingredients. See the end of this leaflet for a complete list of ingredients.
- are allergic to tolterodine tartrate tablets or tolterodine tartrate extended-release capsules.
- are not able to empty your bladder (urinary retention).
- have delayed or slow emptying of your stomach (gastric retention).
- have an eye problem called uncontrolled narrow-angle glaucoma.

Before you take TOVIAZ, tell your healthcare provider about all your medical conditions, including if you:

- have problems emptying your bladder or you have a weak urine stream.
- have any stomach or intestinal problems, or problems with constipation.
- are receiving treatment for an eye problem called narrow-angle glaucoma.
- have a condition called Myasthenia Gravis.
- have kidney problems.
- have liver problems.
- are pregnant or plan to become pregnant. It is not known if TOVIAZ will harm your unborn baby. Talk to your healthcare provider if you are pregnant or plan to become pregnant.
- are breastfeeding or plan to breastfeed. It is not known if TOVIAZ passes into your breast milk. You should talk to your healthcare provider about the best way to feed your baby while taking TOVIAZ.

Tell your healthcare provider about all the medicines you take, including prescription and over-the-counter medicines, vitamins, and herbal products. TOVIAZ may affect the way other medicines work, and other medicines may affect how TOVIAZ works. Especially tell your healthcare provider if you are taking antimuscarinic, antibiotics, or antifungal medicines.
Know all the medicines you take. Keep a list of them with you to show your healthcare provider and pharmacist each time you get a new medicine.

How should I take TOVIAZ?

- Take TOVIAZ exactly as your healthcare provider tells you to take it.
- Your healthcare provider may lower your dose of TOVIAZ if you are an adult with severe kidney problems.
- Your healthcare provider may lower or stop your dose of TOVIAZ if you are a child 6 years of age and older with a body weight greater than 77 pounds (35 kg) and have severe kidney problems or are taking certain medicines.
- Take TOVIAZ with liquid and swallow the tablet whole. Do not chew, divide, or crush the tablet.
- Take TOVIAZ with or without food.
- If you miss a dose of TOVIAZ, begin taking TOVIAZ again the next day. Do not take 2 doses of TOVIAZ in the same day.
- If you take too much TOVIAZ, call your healthcare provider or go to an emergency department right away.

What should I avoid while taking TOVIAZ?

- TOVIAZ can cause blurred vision, dizziness, and drowsiness. Do not drive, operate machinery, or do other dangerous activities until you know how TOVIAZ affects you.
- Use caution in hot environments. Decreased sweating and severe heat illness can happen when medicines such as TOVIAZ are used in a hot environment.
- Drinking alcohol while taking medicines such as TOVIAZ may cause increased drowsiness.

What are the possible side effects of TOVIAZ?
TOVIAZ may cause serious side effects, including:

- serious allergic reactions. Symptoms of a serious allergic reaction may include swelling of the face, lips, throat, or tongue. If you have any of these symptoms, you should stop taking TOVIAZ and get emergency medical help right away.
- inability to empty bladder (urinary retention). TOVIAZ may increase your chances of not being able to empty your bladder if you have bladder outlet obstruction. Tell your healthcare provider right away if you are unable to empty your bladder.
- central nervous system (CNS) effects. Talk to your healthcare provider right away if you get any of these side effects: headache, dizziness, and drowsiness.
- worsening of Myasthenia Gravis symptoms.

The most common side effects of TOVIAZ in adults include:

- dry mouth
- constipation

The most common side effects of TOVIAZ in children 6 years of age and older include:

- diarrhea
- urinary tract infection

- dry mouth
- constipation

- stomach pain
- nausea

- weight gain
- headache

Talk to your healthcare provider about any side effect that bothers you or that does not go away. These are not all the possible side effects of TOVIAZ. Call your healthcare provider for medical advice about side effects. You may report side effects to FDA at 1-800-FDA-1088.

How should I store TOVIAZ?

- Store TOVIAZ at room temperature between 68° to 77°F (20° to 25°C).
- Protect the medicine from moisture by keeping the bottle closed tightly.
- Keep TOVIAZ and all medicines out of the reach of children.

General information about the safe and effective use of TOVIAZ.
Medicines are sometimes prescribed for purposes other than those listed in a Patient Information leaflet. Do not use TOVIAZ for a condition for which it was not prescribed. Do not give TOVIAZ to other people, even if they have the same symptoms you have. It may harm them. You can ask your pharmacist or healthcare provider for information about TOVIAZ that is written for health professionals.

What are the ingredients in TOVIAZ?
Active ingredient: fesoterodine fumarate.
Inactive ingredients: glyceryl behenate, hypromellose, indigo carmine aluminum lake, lactose monohydrate, soya lecithin, microcrystalline cellulose, polyethylene glycol, polyvinyl alcohol, talc, titanium dioxide, and xylitol.
This product's labeling may have been updated. For the most recent prescribing information, please visit www.pfizer.com.

LAB-0382-14.0
For more information, go to www.TOVIAZ.com or call 1-877-9-TOVIAZ (1-877)-986-8429.

This Patient Information has been approved by the U.S. Food and Drug Administration.

Revised: 2/2024

PRINCIPAL DISPLAY PANEL - 4 mg Tablet Bottle Label

NDC 0069-0242-30

30 Tablets
Rx only

Toviaz®
(fesoterodine fumarate)
extended release tablets

4 mg

Pfizer
Distributed by
Pfizer Labs
Division of Pfizer Inc.
New York, NY 10001

PRINCIPAL DISPLAY PANEL - 8 mg Tablet Bottle Label

NDC 0069-0244-30

30 Tablets
Rx only

Toviaz®
(fesoterodine fumarate)
extended release tablets

8 mg

Pfizer
Distributed by
Pfizer Labs
Division of Pfizer Inc.
New York, NY 10001